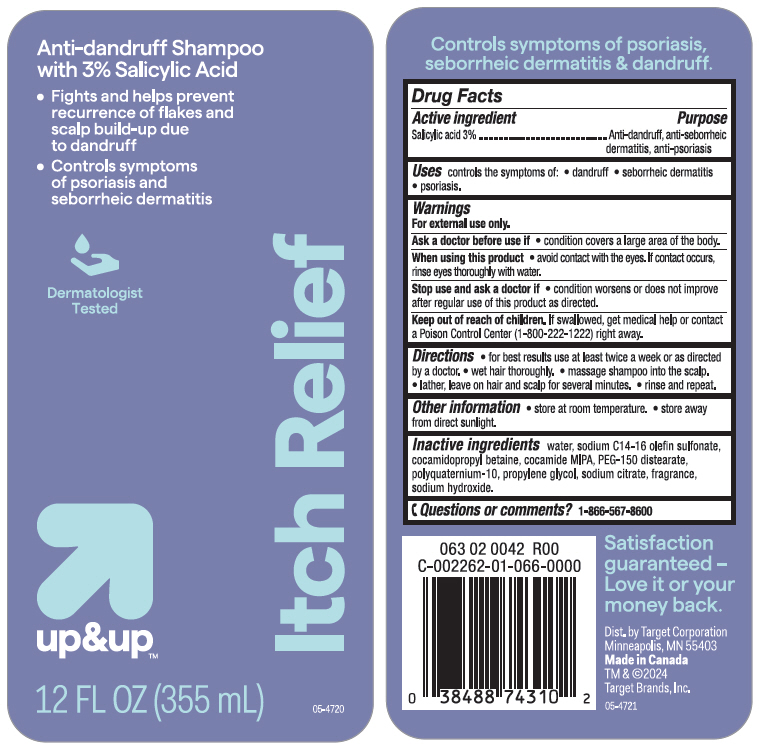 DRUG LABEL: upandup Anti-dandruff with Salicylic Acid
NDC: 82442-743 | Form: SHAMPOO
Manufacturer: TARGET CORPORATION
Category: otc | Type: HUMAN OTC DRUG LABEL
Date: 20240520

ACTIVE INGREDIENTS: SALICYLIC ACID 30 mg/1 mL
INACTIVE INGREDIENTS: Water; Sodium C14-16 Olefin Sulfonate; Cocamidopropyl Betaine; COCO MONOISOPROPANOLAMIDE; PEG-150 Distearate; POLYQUATERNIUM-10 (30000 MPA.S AT 2%); Propylene Glycol; SODIUM CITRATE, UNSPECIFIED FORM; Sodium Hydroxide

up&up™ Anti-dandruff Shampoo with 3% Salicylic Acid
Anti-dandruff, anti-seborrheic dermatitis, anti-psoriasis

Drug Facts

Active ingredient

Salicylic acid 3.0%

Purpose

Anti-dandruff, anti-seborrheic dermatitis, anti-psoriasis

Uses

controls the symptom of:

- dandruff
- seborrheic dermatitis
- psoriasis

Warnings

For external use only.

Ask a doctor before use if you have a condition that covers a large area of the body.

When using this product

- avoid contact with eyes. If contact occurs, rinse eyes thoroughly with water.

Stop use and ask a doctor if

- condition worsens or does not improve after regular use of this product as directed.

Keep out of reach of children. If swallowed, get medical help or contact a Poison Control Center (1-800-222-1222) right away.

Directions

- for best results use at least twice a week or as directed by a doctor.
- wet hair thoroughly.
- massage shampoo into the scalp.
- lather, leave on hair and scalp for several minutes.
- rinse and repeat.

Other information

- store at room temperature
- store away from direct sunlight.

Inactive ingredients

water, sodium C14-16 olefin sulfonate, cocamidopropyl betaine, cocamide MIPA, PEG-150 distearate, polyquaternium-10, propylene glycol, sodium citrate, fragrance, sodium hydroxide.

Questions or comments?

1-866-567-8600

Dist. by Target Corporation
Minneapolis, MN 55403

PRINCIPAL DISPLAY PANEL - 355 mL Bottle Label

Anti-dandruff Shampoo
with 3% Salicylic Acid

- Fights and helps prevent
  recurrence of flakes and
  scalp build-up due
  to dandruff
- Controls symptoms
  of psoriasis and
  seborrheic dermatitis

Dermatologist
Tested

up&up™

12 FL OZ (355 mL)

Itch Relief

05-4720